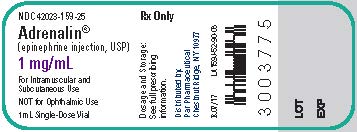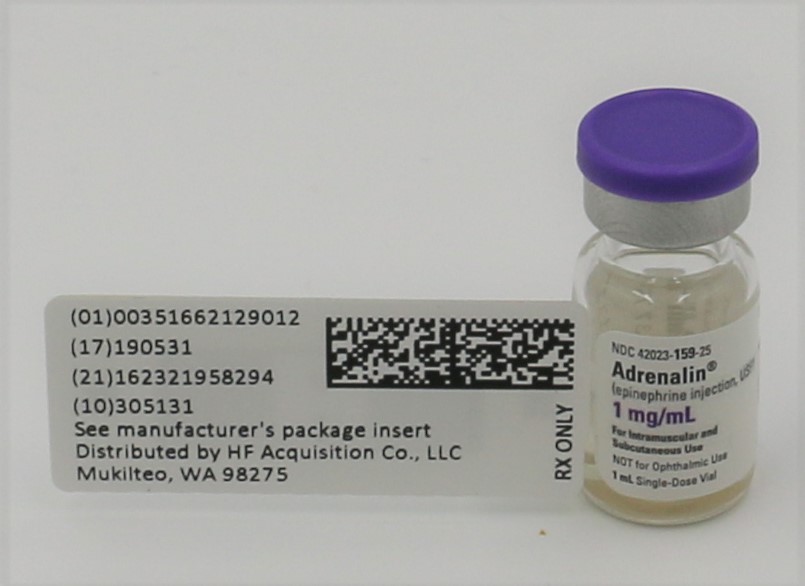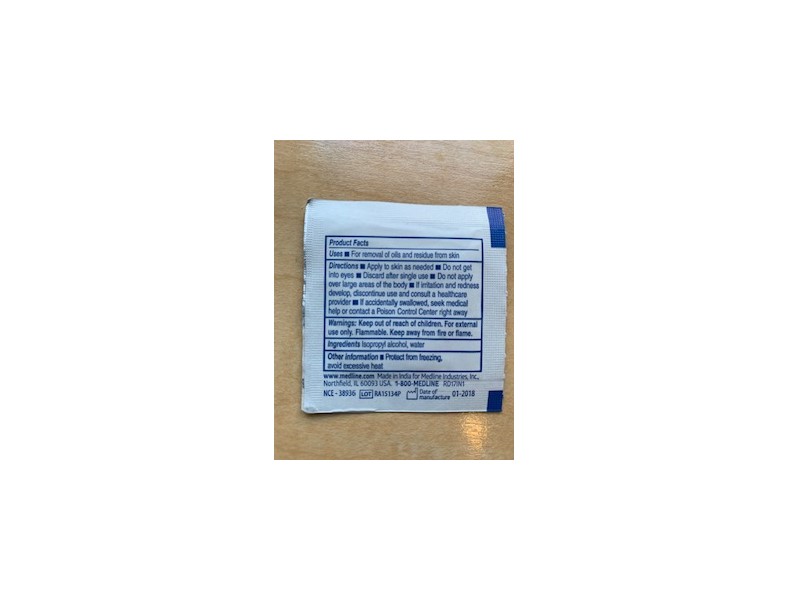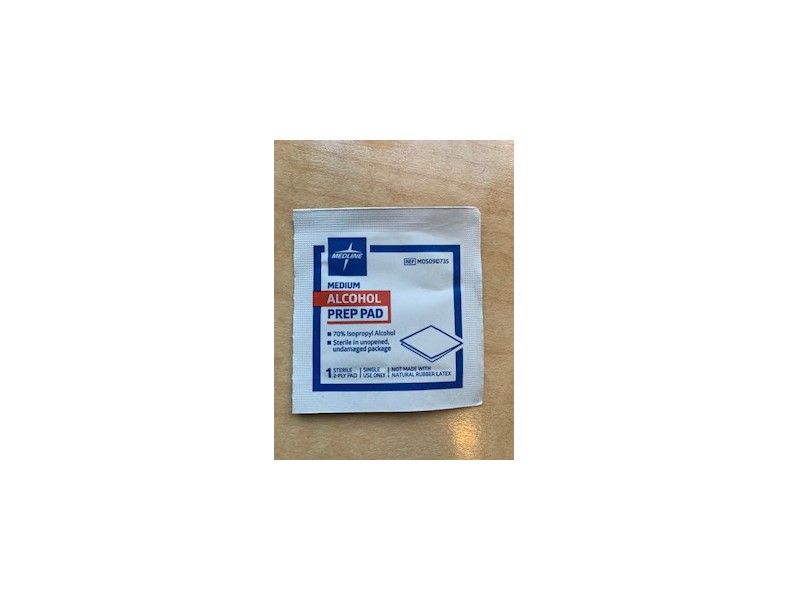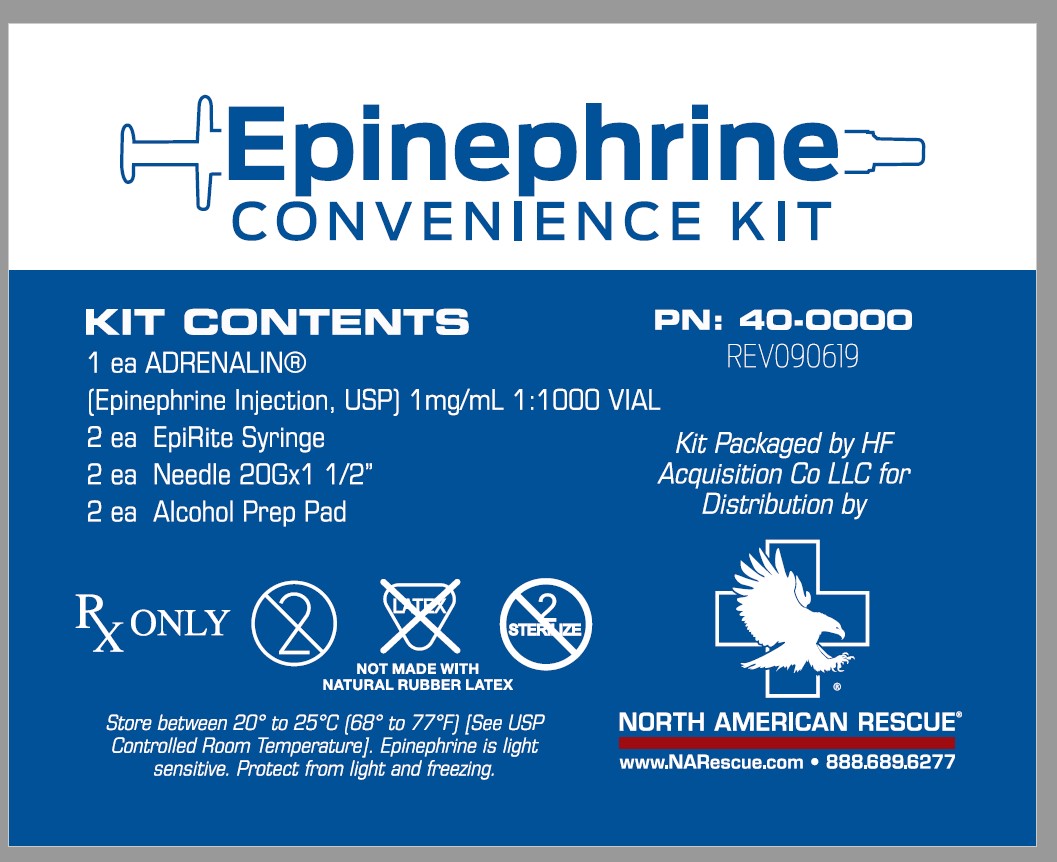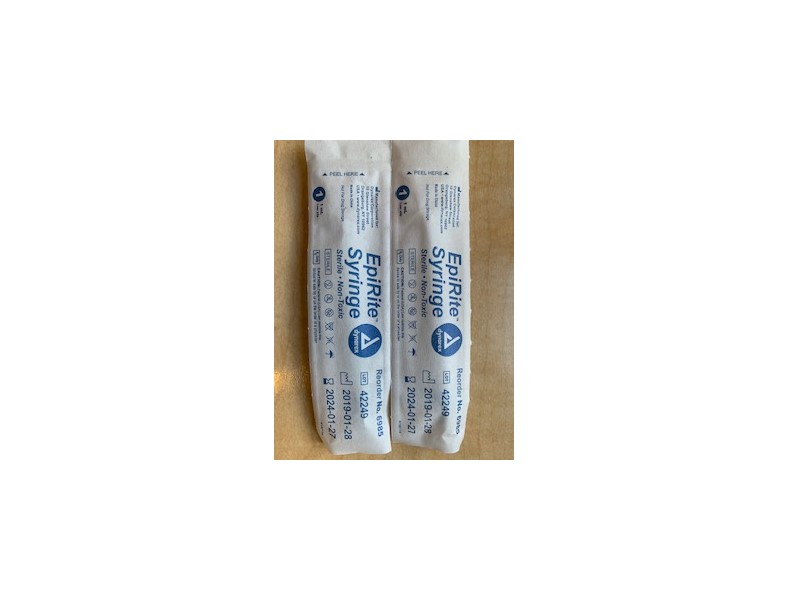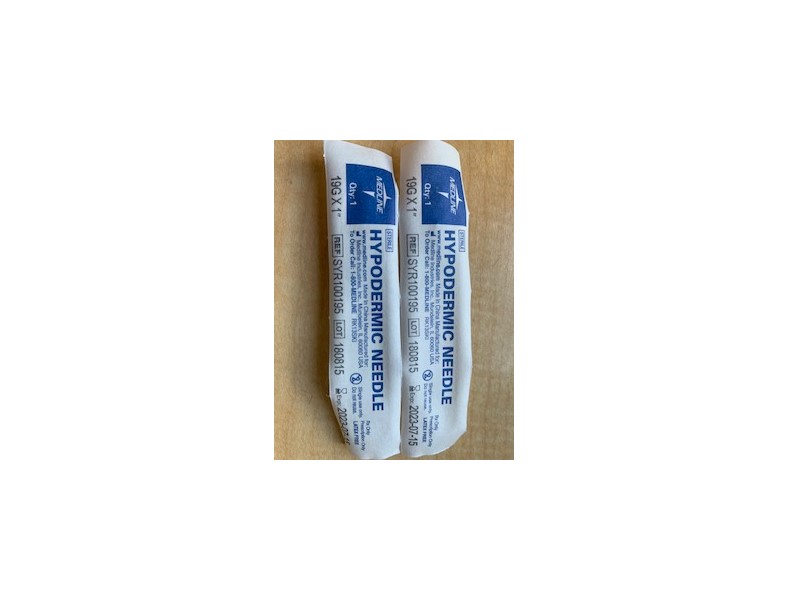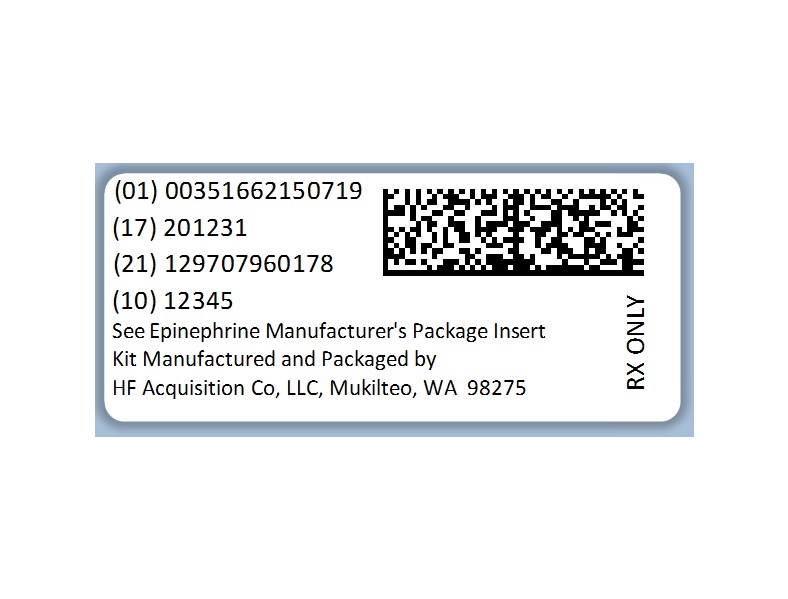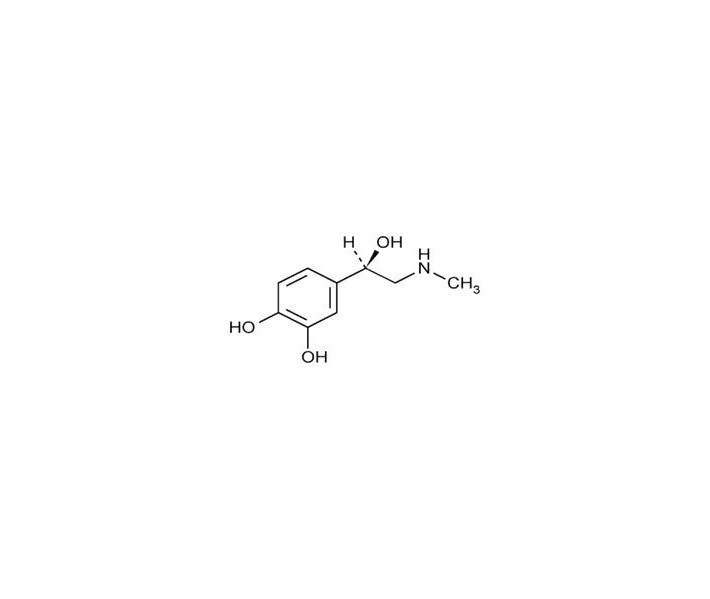 DRUG LABEL: Epinephrine Convenience Kit
NDC: 51662-1507 | Form: KIT | Route: INTRAMUSCULAR
Manufacturer: HF Acquisition Co LLC, DBA HealthFirst
Category: prescription | Type: HUMAN PRESCRIPTION DRUG LABEL
Date: 20250108

ACTIVE INGREDIENTS: EPINEPHRINE 1 mg/1 mL
INACTIVE INGREDIENTS: SODIUM HYDROXIDE 1 mg/1 mL; HYDROCHLORIC ACID; SODIUM METABISULFITE 0.457 mg/1 mL; WATER; TARTARIC ACID 2.25 mg/1 mL; EDETATE DISODIUM 0.2 mg/1 mL; SODIUM CHLORIDE 7.3 mg/1 mL

EPINEPHRINE CONVENIENCE KIT

HIGHLIGHTS OF PRESCRIBING INFORMATION

These highlights do not include all the information needed to use ADRENALIN safely and effectively. See full prescribing information for ADRENALIN.
ADRENALIN (epinephrine injection) 1 mg/mL, for
intramuscular, subcutaneous, and intravenous use
Initial U.S. Approval: 1939

RECENT MAJOR CHANGES

Indications and Usage (1.2) 01/2019

Dosage and Administration (2.3) 01/2019

Warnings and Precautions (5.3, 5.4, 5.5, 5.6, 5.7) 01/2019

INDICATIONS AND USAGE

Adrenalin® is a non-selective alpha and beta adrenergic agonist indicated for:

Emergency treatment of allergic reactions (Type 1), including anaphylaxis (1-1.1)
To increase mean arterial blood pressure in adult patients with hypotension associated with septic shock (1-1.2)

DOSAGE AND ADMINISTRATION

Anaphylaxis:

Adults and Children 30 kg (66 lbs) or more: 0.3 mg to 0.5 mg (0.3 mL to 0.5 mL) intramuscularly or subcutaneously into anterolateral aspect of the thigh every 5 to 10 minutes as necessary (2-2.2)
Children 30 kg (66 lbs) or less: 0.01 mg/kg (0.01 mL/kg), up to 0.3 mg (0.3 mL), intramuscularly or subcutaneously into anterolateral aspect of the thigh every 5 to 10 minutes as necessary (2-2.2)

Hypotension associated with septic shock:

Dilute epinephrine in dextrose solution prior to infusion (2-2.3)
Infuse epinephrine into a large vein (2-2.3)
Intravenous infusion rate of 0.05 mcg/kg/min to 2 mcg/kg/min, titrated to achieve desired mean arterial pressure (2-2.3)
Wean gradually (2-2.3)
See Full Prescribing Information for instructions on dilution and administration of the injection.

DOSAGE FORMS AND STRENGTHS

Injection: 1 mg/mL single dose vial and 30 mg/30 mL (1 mg/mL) multiple dose vial (3)

CONTRAINDICATIONS

None (4)

WARNINGS AND PRECAUTIONS

Do not inject into buttocks, digits, hands, or feet (5-5.1)
Avoid extravasation into tissues, which can cause local necrosis (5-5.3)
May aggravate angina pectoris or produce ventricular arrhythmias (5-5.7)

ADVERSE REACTIONS

Common adverse reactions to systemically administered epinephrine include anxiety, tremor, weakness, dizziness, sweating, palpitations and pallor (6)

To report SUSPECTED ADVERSE REACTIONS, contact Par Pharmaceutical at 1-800-828-9393 or FDA at 1-800-FDA-1088 or www.fda.gov/medwatch.

DRUG INTERACTIONS

Drugs that counter the pressor effects of epinephrine include alpha blockers, vasodilators such as nitrates, diuretics, antihypertensives and ergot alkaloids. (7-7.1)
Drugs that potentiate the effects of epinephrine include sympathomimetics, beta blockers, tricyclic antidepressants, MAO inhibitors, COMT inhibitors, clonidine, doxapram, oxytocin, levothyroxine sodium, quinidine and certain antihistamines. (7-7.2)
Drugs that increase the arrhythmogenic potential of epinephrine include beta blockers, cyclopropane and halogenated hydrocarbon anesthetics, antihistamines, exogenous thyroid hormones, diuretics, and cardiac glycosides. Observe for development of cardiac arrhythmias. (7-7.3)
Potassium-depleting drugs, including corticosteroids, diuretics, and theophylline, potentiate the hypokalemic effects of epinephrine. (7-7.4)

USE IN SPECIFIC POPULATIONS

Elderly patients and pregnant women may be at greater risk of developing adverse reactions when epinephrine is administered parenterally (8-8.1, 8-8.5)
Pregnancy: May cause fetal harm (8-8.1)

See 17 for PATIENT COUNSELING INFORMATION.

Revised: 1/2019

KIT CONTENTS

Item #1007670-ADRENALIN® (EPINEPHRINE INJECTION, USP) 1mg/mL 1:1000 VIAL, NDC 51662-1290-1, 2 Total

Item # 6985-EpiRite Syringe, 2 Total

Item # 1005310-Needle 20Gx1 1/2", 2 Total

N/A-Alcohol Prep Pad, 2 Total

N/A- Package Insert, 1 Total

1 INDICATIONS & USAGE

Adrenalin® is available as a single-use 1 mL vial and a multiple-use 30 mL vial for intramuscular and subcutaneous use.

Emergency treatment of allergic reactions (Type I), including anaphylaxis, which may result from allergic reactions to insect stings, biting insects, foods, drugs, sera, diagnostic testing substances and other allergens, as well as idiopathic anaphylaxis or exercise-induced anaphylaxis. The signs and symptoms associated with anaphylaxis include flushing, apprehension, syncope, tachycardia, thready or unobtainable pulse associated with hypotension, convulsions, vomiting, diarrhea and abdominal cramps, involuntary voiding, airway swelling, laryngospasm, bronchospasm, pruritus, urticaria or angioedema, swelling of the eyelids, lips, and tongue.

2 DOSAGE & ADMINISTRATIN

Inject Adrenalin® intramuscularly or subcutaneously into the anterolateral aspect of the thigh, through clothing if necessary. When administering to a child, to minimize the risk of injection related injury, hold the leg firmly in place and limit movement prior to and during an injection. The injection may be repeated every 5 to 10 minutes as necessary. For intramuscular administration, use a needle long enough (at least 1/2 inch to 5/8 inch) to ensure the injection is administered into the muscle. Monitor the patient clinically for the severity of the allergic reaction and potential cardiac effects of the drug, with repeat doses titrated to effect. Do not administer repeated injections at the same site, as the resulting vasoconstriction may cause tissue necrosis.

Inspect visually for particulate matter and discoloration prior to administration. Do not use if the solution is colored or cloudy, or if it contains particulate matter.

Adults and Children 30 kg (66 lbs) or more: 0.3 to 0.5 mg (0.3 mL to 0.5 mL) of undiluted Adrenalin® administered intramuscularly or subcutaneously in the anterolateral aspect of the thigh, up to a maximum of 0.5 mg (0.5 mL) per injection, repeated every 5 to 10 minutes as necessary. Monitor clinically for reaction severity and cardiac effects.

Children less than 30 kg (66 lbs): 0.01 mg/kg (0.01 mL/kg) of undiluted Adrenalin® administered intramuscularly or subcutaneously in the anterolateral aspect of the thigh, up to a maximum of 0.3 mg (0.3 mL) per injection, repeated every 5 to 10 minutes as necessary. Monitor clinically for reaction severity and cardiac effects.

3 DOSAGE FORMS & STRENGTHS

Adrenalin® 1 mg/mL epinephrine injection, 1 mL solution in a single-use clear glass vial

4 CONTRAINDICATIONS

None.

5 WARNINGS AND PRECAUTIONS

5.1 Incorrect Locations of Injection

Injection into the anterolateral aspect of the thigh (vastus lateralis muscle) is the most appropriate location for administration because of its location, size, and available blood flow. Injection into (or near) smaller muscles, such as in the deltoid, is not recommended due to possible differences in absorption associated with this use.

Do not administer repeated injections of epinephrine at the same site, as the resulting vasoconstriction may cause tissue necrosis.

Do not inject into buttock. Injection into the buttock may not provide effective treatment of anaphylaxis and has been associated with the development of Clostridial infections (gas gangrene). Cleansing with alcohol does not kill bacterial spores, and therefore, does not lower this risk.

Do not inject into digits, hands, or feet. Epinephrine is a strong vasoconstrictor. Accidental injection into the digits, hands or feet may result in loss of blood flow to the affected area and has been associated with tissue necrosis.

5.2 Serious Infections at the Injection Site

Rare cases of serious skin and soft tissue infections, including necrotizing fasciitis and myonecrosis caused by Clostridia (gas gangrene), have been reported at the injection site following epinephrine injection for anaphylaxis. Clostridium spores can be present on the skin and introduced into the deep tissue with subcutaneous or intramuscular injection. While cleansing with alcohol may reduce presence of bacteria on the skin, alcohol cleansing does not kill Clostridium spores. To decrease the risk of Clostridium infection, do not inject Adrenalin® into the buttock [see Warnings and Precautions (5.1)]. Advise patients to seek medical care if they develop signs or symptoms of infection, such as persistent redness, warmth, swelling, or tenderness, at the epinephrine injection site.

5.3 Disease Interactions

Some patients may be at greater risk for developing adverse reactions after systemic epinephrine administration. Despite these concerns, the presence of these conditions is not a contraindication to epinephrine administration in an acute, life-threatening situation.

Patients with Heart Disease

Epinephrine should be administered with caution in patients who have heart disease, including patients with cardiac arrhythmias, coronary artery or organic heart disease, cerebrovascular disease, or hypertension. In such patients, or in patients who are on drugs that may sensitize the heart to arrhythmias, epinephrine may precipitate or aggravate angina pectoris as well as produce ventricular arrhythmias [see Drug Interactions (7) and Adverse Reactions (6)].

Other Patients and Diseases

Epinephrine should be administered with caution to patients with hyperthyroidism, Parkinson's disease, diabetes mellitus, pheochromocytoma, elderly individuals, and pregnant women. Patients with Parkinson's disease may experience psychomotor agitation or notice a temporary worsening of symptoms. Diabetic patients may experience transient increases in blood sugar.

5.4 Allergic Reactions Associated with Sulfite

Adrenalin® contains sodium bisulfite which may cause mild to severe allergic reactions including anaphylaxis or asthmatic episodes in susceptible individuals. However, the presence of bisulfite in this product should not preclude its use for the treatment of serious allergic or other emergency situations even if the patient is sulfite-sensitive, as the alternatives to using epinephrine in a life-threatening situation may not be satisfactory.

6 ADVERSE REACTIONS

Common adverse reactions to systemically administered epinephrine include anxiety, apprehensiveness, restlessness, tremor, weakness, dizziness, sweating, palpitations, pallor, nausea and vomiting, headache, and respiratory difficulties. These symptoms occur in some persons receiving therapeutic doses of epinephrine, but are more likely to occur in patients with heart disease, hypertension, or hyperthyroidism [see Warnings and Precautions 5-(5.3)].

Due to the lack of randomized, controlled clinical trials of epinephrine for the treatment of anaphylaxis, the true incidence of adverse reactions associated with the systemic use of epinephrine is difficult to determine. Adverse reactions reported in observational trials, case reports, and studies are listed below by body system:

Cardiovascular: angina, arrhythmias, hypertension, pallor, palpitations, tachyarrhythmia, tachycardia, vasoconstriction, ventricular ectopy and stress cardiomyopathy.

Angina may occur in patients with coronary artery disease [see Warnings and Precautions 5-(5.3)].

Arrhythmias, including fatal ventricular fibrillation, have occurred, particularly in patients with underlying organic heart disease or patients receiving drugs that sensitize the heart to arrhythmias [see Warnings and Precautions 5-(5.3)].

Rapid rises in blood pressure associated with epinephrine use have produced cerebral hemorrhage, particularly in elderly patients with cardiovascular disease [see Warnings and Precautions 5-(5.3)].

Respiratory: respiratory difficulties.

Neurological: dizziness , disorientation , excitability , headache , impaired memory , lightheadedness , nervousness , panic, psychomotor agitation, sleepiness , tingling , tremor, and weakness.

Psychiatric: anxiety, apprehensiveness, restlessness.

Gastrointestinal: nausea, vomiting.

Other:

Patients with Parkinson's disease may experience psychomotor agitation or a temporary worsening of symptoms [see Warnings and Precautions 5-(5.3)].

Diabetic patients may experience transient increases in blood sugar [see Warnings and Precautions 5-(5.3)].

Accidental injection into the digits, hands or feet may result in loss of blood flow to the affected area [see Warnings and Precautions 5-(5.1)]. Adverse events experienced as a result of an injection into these areas include increased heart rate, local reactions including injection site pallor, coldness, hypoesthesia, and tissue loss, or injury at the injection site resulting in bruising, bleeding, discoloration, erythema, and skeletal injury.

Injection into the buttock has resulted in cases of gas gangrene [see Warnings and Precautions 5-(5.1)].

Rare cases of serious skin and soft tissue infections, including necrotizing fasciitis and myonecrosis caused by Clostridia (gas gangrene), have been reported following epinephrine injection in the thigh [see Warnings and Precautions 5-(5.2)].

Skin: sweating.

To report SUSPECTED ADVERSE REACTIONS, contact Par Pharmaceutical at 1-800-828-9393 or FDA at 1-800-FDA-1088 or www.fda.gov/medwatch.

7 DRUG INTERACTIONS

Epinephrine should be administered cautiously to patients taking other sympathomimetic agents because of the possibility of additive effects.

Patients who are concomitantly receiving cardiac glycosides, digitalis, diuretics, quinidine, and other antiarrhythmics should be observed carefully for the development of cardiac arrhythmias [see Warnings and Precautions 5-(5.3) and Adverse Reactions (6)].

Administer epinephrine cautiously to patients receiving halogenated hydrocarbon general anesthetics, such as halothane, as coadministration may result in arrhythmias.

The effects of epinephrine may be potentiated by tricyclic antidepressants such as imipramine, monoamine oxidase inhibitors (MAOI), levothyroxine sodium, and certain antihistamines, notably diphenhydramine, tripelannamine, and dexchlorpheniramine.

The cardiostimulating and bronchodilating effects of epinephrine are antagonized by beta-adrenergic blocking drugs, such as propranolol.

The vasoconstricting and hypertensive effects of epinephrine are antagonized by alpha-adrenergic blocking drugs, such as phentolamine.

Ergot alkaloids may reverse the pressor effects of epinephrine.

Epinephrine should not be used to counteract circulatory collapse or hypotension caused by phenothiazines, as a reversal of the pressor effects of epinephrine may result in further lowering of blood pressure.

8 USE IN SPECIFIC POPULATIONS

8.1 Pregnancy

Teratogenic Effects: Pregnancy Category C.

There are no adequate and well-controlled studies in pregnant women. Epinephrine should be used during pregnancy only if the potential benefit justifies the potential risk to the fetus (fetal anoxia, spontaneous abortion, or both). Epinephrine is teratogenic in rabbits, mice and hamsters dosed during organogenesis.

Epinephrine has been shown to have teratogenic effects (including gastroschisis and embryonic lethality) when administered subcutaneous in rabbits at approximately 15 times the maximum recommended intramuscular or subcutaneous dose (on a mg/m2 basis at a maternal subcutaneous dose of 1.2 mg/kg/day for two to three days).

In mice, teratogenic effects (including embryonic lethality) were observed at approximately 3 times the maximum recommended intramuscular or subcutaneous dose (on a mg/m2 basis at maternal subcutaneous dose of 1 mg/kg/day for 10 days). These effects were not seen in mice at approximately 2 times the maximum recommended daily intramuscular or subcutaneous dose (on a mg/m2 basis at a subcutaneous maternal dose of 0.5 mg/kg/day for 10 days).

In hamsters, teratogenic effects were observed at approximately 2 times the maximum recommended intramuscular or subcutaneous dose (on a mg/m2 basis at a maternal subcutaneous dose of 0.5 mg/kg/day for 4 days).

8.2 Labor and Delivery

Use with caution during labor and delivery. Although epinephrine improves maternal hypotension associated with anaphylaxis, it may result in uterine vasoconstriction, decreased uterine blood flow, and fetal anoxia.

8.3 Nursing Mothers

It is not known whether epinephrine is excreted in human milk. Because many drugs are excreted in human milk, caution should be exercised when epinephrine is administered to a nursing woman.

8.4 Pediatric Use

Clinical use data support weight-based dosing for treatment of anaphylaxis in pediatric patients, and other reported clinical experience with the use of epinephrine suggests that the adverse reactions seen in children are similar in nature and extent to those both expected and reported in adults.

8.5 Geriatric Use

Clinical studies for the treatment of anaphylaxis have not been performed in subjects aged 65 and over to determine whether they respond differently from younger subjects. However, other reported clinical experience with use of epinephrine for the treatment of anaphylaxis has identified that geriatric patients may be particularly sensitive to the effects of epinephrine. Therefore, for the treatment of anaphylaxis, consider starting with a lower dose to take into account potential concomitant disease or other drug therapy.

10 OVERDOSAGE

Overdosage of epinephrine may produce extremely elevated arterial pressure, which may result in cerebrovascular hemorrhage, particularly in elderly patients. Overdosage may also result in pulmonary edema because of peripheral vascular constriction together with cardiac stimulation. Treatment consists of a rapidly acting α-adrenergic blocking drug and respiratory support.

Epinephrine is rapidly inactivated in the body and treatment following overdose with epinephrine is primarily supportive. If necessary, pressor effects may be counteracted by rapidly acting vasodilators or α-adrenergic blocking drugs. If prolonged hypotension follows such measures, it may be necessary to administer another pressor drug.

Epinephrine overdosage can also cause transient bradycardia followed by tachycardia and these may be accompanied by potentially fatal cardiac arrhythmias. Premature ventricular contractions may appear within one minute after injection and may be followed by multifocal ventricular tachycardia (prefibrillation rhythm). Subsidence of the ventricular effects may be followed by atrial tachycardia and occasionally by atrioventricular block. Treatment of arrhythmias consists of administration of a beta-adrenergic blocking drug such as propranolol.

Overdosage sometimes results in extreme pallor and coldness of the skin, metabolic acidosis due to elevated blood lactic acid levels, and kidney failure. Suitable corrective measures must be taken in such situations.

Myocardial ischemia, myocardial infarction and cardiomyopathy have been noted in the literature following overdose of epinephrine.

11 DESCRIPTION

Adrenalin® (epinephrine injection, USP) is a clear, colorless, sterile solution containing 1 mg/mL epinephrine, packaged as 1 mL of solution in a single-use clear glass vial or 30 mL of solution in a multiple-dose amber glass vial. In the 1 mL vial, each 1 mL of Adrenalin® solution contains 1 mg epinephrine, 7.3 mg sodium chloride, 0.457 mg sodium metabisulfite, 1 mg sodium hydroxide, 2.25 mg tartaric acid, 0.20 mg disodium edetate dihydrate, hydrochloric acid to adjust pH, and water for injection. In the 30 mL vial, each 1 mL of Adrenalin® solution contains 1 mg epinephrine, 6.15 mg sodium chloride, 0.457 mg sodium metabisulfite, 0.920 mg sodium hydroxide, 2.25 mg tartaric acid, 0.20 mg disodium edetate dihydrate, hydrochloric acid to adjust pH, 5.25 mg chlorobutanol as a preservative and water for injection. The pH range is 2.2-5.0.

Epinephrine is a sympathomimetic catecholamine. The chemical name of epinephrine is: 1,2-Benzenediol, 4-[(1R)-1-hydroxy-2-(methylamino)ethyl]-, or (-)-3,4-Dihydroxy-α-[2-(methylamino)ethyl]benzyl alcohol.

The chemical structure of epinephrine is:

The molecular weight of epinephrine is 183.2.

Epinephrine solution deteriorates rapidly on exposure to air or light, turning pink from oxidation to adrenochrome and brown from the formation of melanin.

12 CLINICAL PHARMACOLOGY

12.1 Mechanism of Action

Epinephrine acts on both alpha and beta-adrenergic receptors.

12.2 Pharmacodynamics

Through its action on alpha-adrenergic receptors, epinephrine lessens the vasodilation and increased vascular permeability that occurs during anaphylaxis, which can lead to loss of intravascular fluid volume and hypotension.

Through its action on beta-adrenergic receptors, epinephrine causes bronchial smooth muscle relaxation and helps alleviate bronchospasm, wheezing and dyspnea that may occur during anaphylaxis.

Epinephrine also alleviates pruritus, urticaria, and angioedema and may relieve gastrointestinal and genitourinary symptoms associated with anaphylaxis because of its relaxer effects on the smooth muscle of the stomach, intestine, uterus and urinary bladder.

Epinephrine increases glycogenolysis, reduces glucose up take by tissues, and inhibits insulin release in the pancreas, resulting in hyperglycemia and increased blood lactic acid [see Warnings and Precautions 5-(5.3)].

Epinephrine causes mydriasis when administered parenterally.

12.3 Pharmacokinetics

When administered parenterally, epinephrine has a rapid onset and short duration of action.

13 NONCLINICAL TOXICOLOGY

13.1 Carcinogenesis, Mutagenesis, Impairment of Fertility

Long- term studies to evaluate the carcinogenic potential of epinephrine have not been conducted.

Epinephrine and other catecholamines have been shown to have mutagenic potential in vitro. Epinephrine was positive in the Salmonella bacterial reverse mutation assay, positive in the mouse lymphoma assay, and negative in the in vivo micronucleus assay. Epinephrine is an oxidative mutagen based on the E. coli WP2 Mutoxitest bacterial reverse mutation assay. This should not prevent the use of epinephrine under the conditions noted under Indications and Usage (1).

The potential for epinephrine to impair reproductive performance has not been evaluated, but epinephrine has been shown to decrease implantation in female rabbits dosed subcutaneously with 1.2 mg/kg/day (15-fold the highest human intramuscular or subcutaneous daily dose) during gestation days 3 to 9.

16 HOW SUPPLIED/STORAGE & HANDLING

Epinephrine Convenience Kit is supplied in the following dosage forms.
NDC 51662-1507-1 (Epinephrine Convenience Kit)
Kit Contains:

Item #1007670-ADRENALIN® (EPINEPHRINE INJECTION, USP) 1mg/mL 1:1000 VIAL, NDC 51662-1290-1, 2 Total

Item # 6985-EpiRite Syringe, 2 Total

Item # 1005310-Needle 20Gx1 1/2", 2 Total

N/A-Alcohol Prep Pad, 2 Total

N/A- Package Insert, 1 Total

HF Acquisition Co LLC, DBA HealthFirst
Mukilteo, WA 98275

Adrenalin® 1 mL Single-Use Vials:

Vial and contents must be discarded 30 days after initial use.

Store between 20° to 25°C (68° to 77°F) [See USP Controlled Room Temperature]. Epinephrine is light sensitive. Protect from light and freezing.

17 PATIENT COUNSELING INFORMATION

Advise patients or their caregivers about common adverse reactions associated with the use of epinephrine including an increase in heart rate, the sensation of a more forceful heartbeat, palpitations, sweating, nausea and vomiting, difficulty breathing, pallor, dizziness, weakness or shakiness, headache, apprehension, nervousness, or anxiety. These symptoms and signs usually subside rapidly, especially with rest, quiet and recumbent positioning.

Warn patients with a good response to initial treatment about the possibility of recurrence of symptoms and instruct patients to obtain proper medical attention if symptoms return.

Warn patients with diabetes that they may develop increased blood glucose levels following epinephrine administration.

Rare cases of serious skin and soft tissue infections, including necrotizing fasciitis and myonecrosis caused by Clostridia (gas gangrene), have been reported at the injection site following epinephrine injection for anaphylaxis. Advise patients to seek medical care if they develop signs or symptoms of infection, such as persistent redness, warmth, swelling, or tenderness, at the epinephrine injection site [see Warnings and Precautions 5-(5.2)].

SPL UNCLASSIFIED

DISTRIBUTED BY

North American Rescue, LLC

35 Tedwall Court
Greer, SC 29650-4791
Phone: 864.675.9800
Fax: 864.675.9880

PRINCIPAL DISPLAY PANEL - EPINEPHRINE KIT LABELING

NDC 51662-1507-1

Principal Display Panel - Serialization Example Labeling

Example of 51662-1507-1 Serialized Labeling